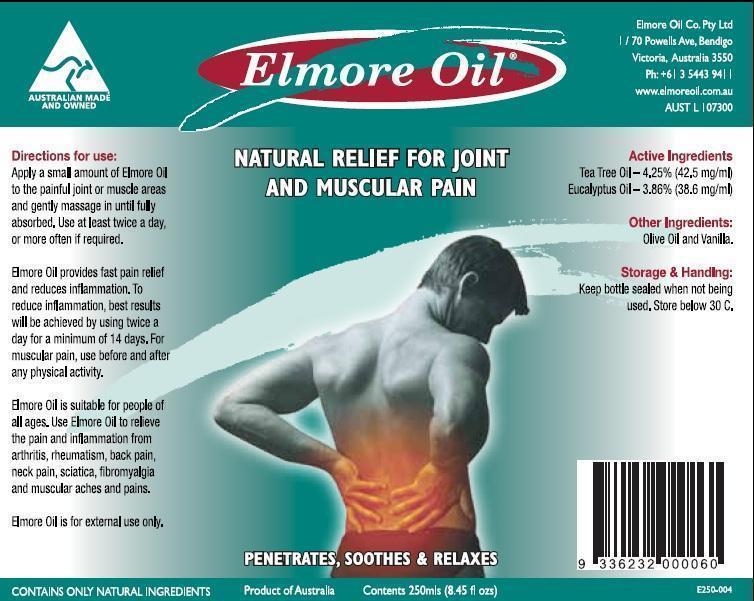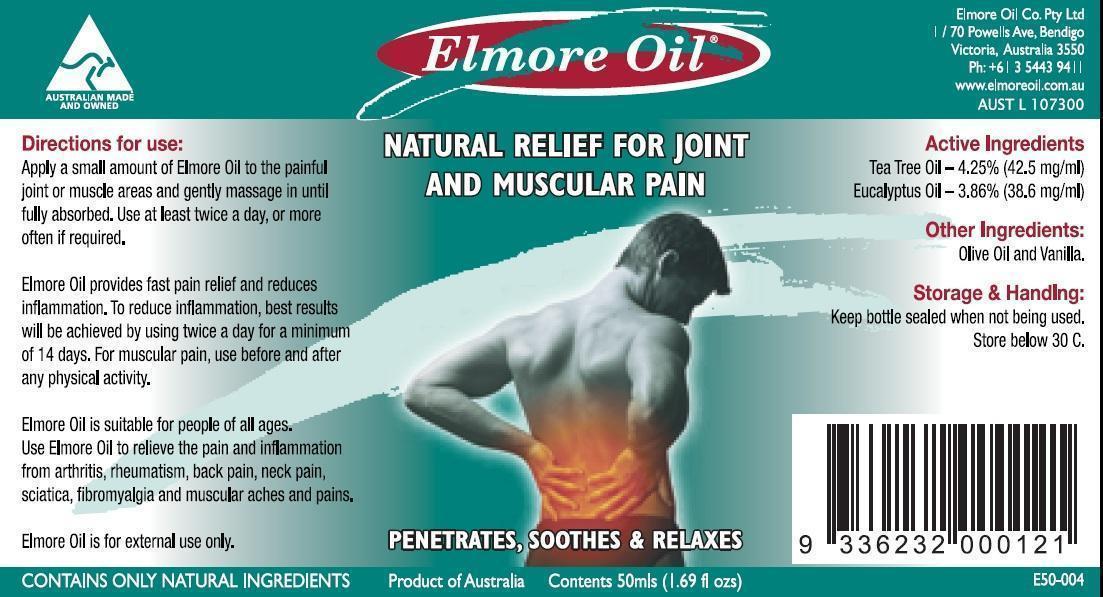 DRUG LABEL: Elmore Oil
NDC: 43979-439 | Form: OIL
Manufacturer: Elmore Oil Company Pty Ltd
Category: otc | Type: HUMAN OTC DRUG LABEL
Date: 20130418

ACTIVE INGREDIENTS: TEA TREE OIL 42.5 mg/1 mL; EUCALYPTUS OIL 38.6 mg/1 mL
INACTIVE INGREDIENTS: Olive Oil

Active Ingredients

Tea Tree Oil (Melaleuca Alternifolia) - 4.25% (42.5 mg/ml)
Eucalyptus Oil (E. Polybractea) - 3.86% (38.6 mg/ml)

Purpose

Massage Oil to assist with relief of joint and muscle pain

Indication and Usage

Temporary relief of joint and muscle pain, including lower back pain

Dosage and Administration

Apply a small amount of Elmore Oil to the pain affected area and gently massage in until fully absorbed. Use before and after activity for maximum relief.

Warnings

For external use only.
In case of accidental ingestion, get medical help or contact a Poisons Control Center right away.

Inactive Ingredients

Olive Oil (INCI name: Olea Europaea (Olive)

Vanilla (INCI Name: Vanillin)

Keep out of Reach of Children